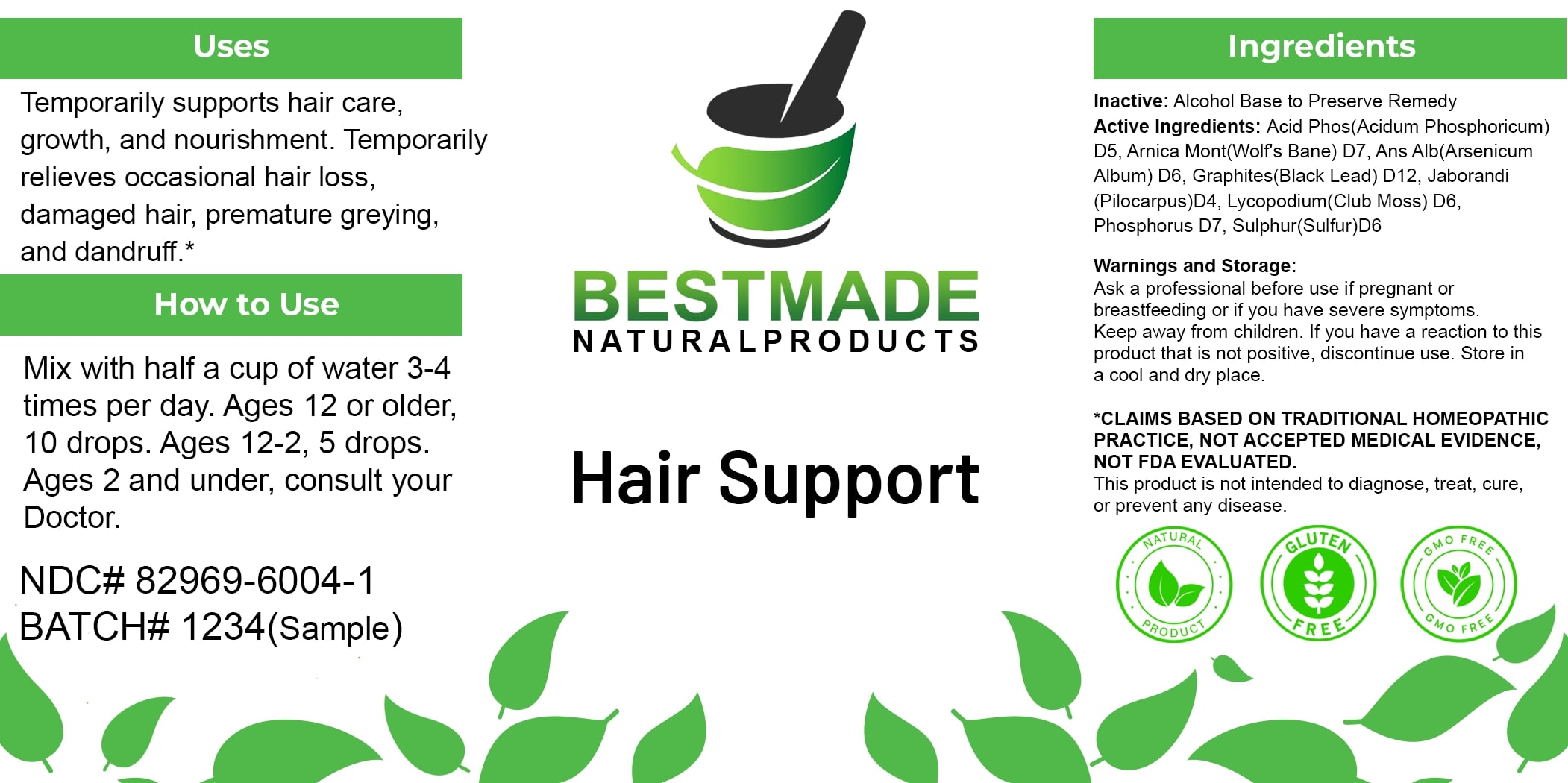 DRUG LABEL: Bestmade Natural Products Hair Support
NDC: 82969-6004 | Form: LIQUID
Manufacturer: Bestmade Natural Products
Category: homeopathic | Type: HUMAN OTC DRUG LABEL
Date: 20250313

ACTIVE INGREDIENTS: LYCOPODIUM CLAVATUM SPORE 30 [hp_C]/30 [hp_C]; PILOCARPUS MICROPHYLLUS LEAF 30 [hp_C]/30 [hp_C]; ARSENIC TRIOXIDE 30 [hp_C]/30 [hp_C]; SULFUR 30 [hp_C]/30 [hp_C]; ARNICA MONTANA 30 [hp_C]/30 [hp_C]; PHOSPHORUS 30 [hp_C]/30 [hp_C]; GRAPHITE 30 [hp_C]/30 [hp_C]; PHOSPHORIC ACID 30 [hp_C]/30 [hp_C]
INACTIVE INGREDIENTS: ALCOHOL 30 [hp_C]/30 [hp_C]

hair support

DOSAGE AND ADMINISTRATION

How to Use

Mix with half a cup of water 3-4 times per day. Ages 12 or older, 10 drops. Ages 12-2, 5 drops. Ages 2 and under, consult your Doctor.

Uses

Temporarily supports hair care, growth, and nourishment. Temporarily relieves occasional hair loss, damaged hair, premature greying, and dandruff.*

*CLAIMS BASED ON TRADITIONAL HOMEOPATHIC PRACTICE, NOT ACCEPTED MEDICAL EVIDENCE, NOT FDA EVALUATED.

This product is not intended to diagnose, treat, cure, or prevent any disease.

Uses

Temporarily supports hair care, growth, and nourishment. Temporarily relieves occasional hair loss, damaged hair, premature greying, and dandruff.*

*CLAIMS BASED ON TRADITIONAL HOMEOPATHIC PRACTICE, NOT ACCEPTED MEDICAL EVIDENCE, NOT FDA EVALUATED.

This product is not intended to diagnose, treat, cure, or prevent any disease.

ACTIVE INGREDIENT

Active Ingredients: Acid Phos(Acidum Phosphoricum) D5, Arnica Mont(Wolf's Bane) D7, Ars Alb(Arsenicum Album) D6, Graphites(Black Lead) D12, Jaborandi(Pilocarpus) D4, Lycopodium(Club Moss) D6, Phosphorus D7, Sulphur(Sulfur) D6

INACTIVE INGREDIENT

Ingredients

Inactive: Alcohol Base to Preserve Remedy

KEEP OUT OF REACH OF CHILDREN

Warnings and Storage:

Ask a professional before use if pregnant or breastfeeding or if you have severe symptoms. Keep away from children. If you have a reaction to this product that is not positive, discontinue use. Store in a cool and dry place.

Warnings and Storage:

Ask a professional before use if pregnant or breastfeeding or if you have severe symptoms. Keep away from children. If you have a reaction to this product that is not positive, discontinue use. Store in a cool and dry place.

*CLAIMS BASED ON TRADITIONAL HOMEOPATHIC PRACTICE, NOT ACCEPTED MEDICAL EVIDENCE, NOT FDA EVALUATED.

This product is not intended to diagnose, treat, cure, or prevent any disease.

Entire package label